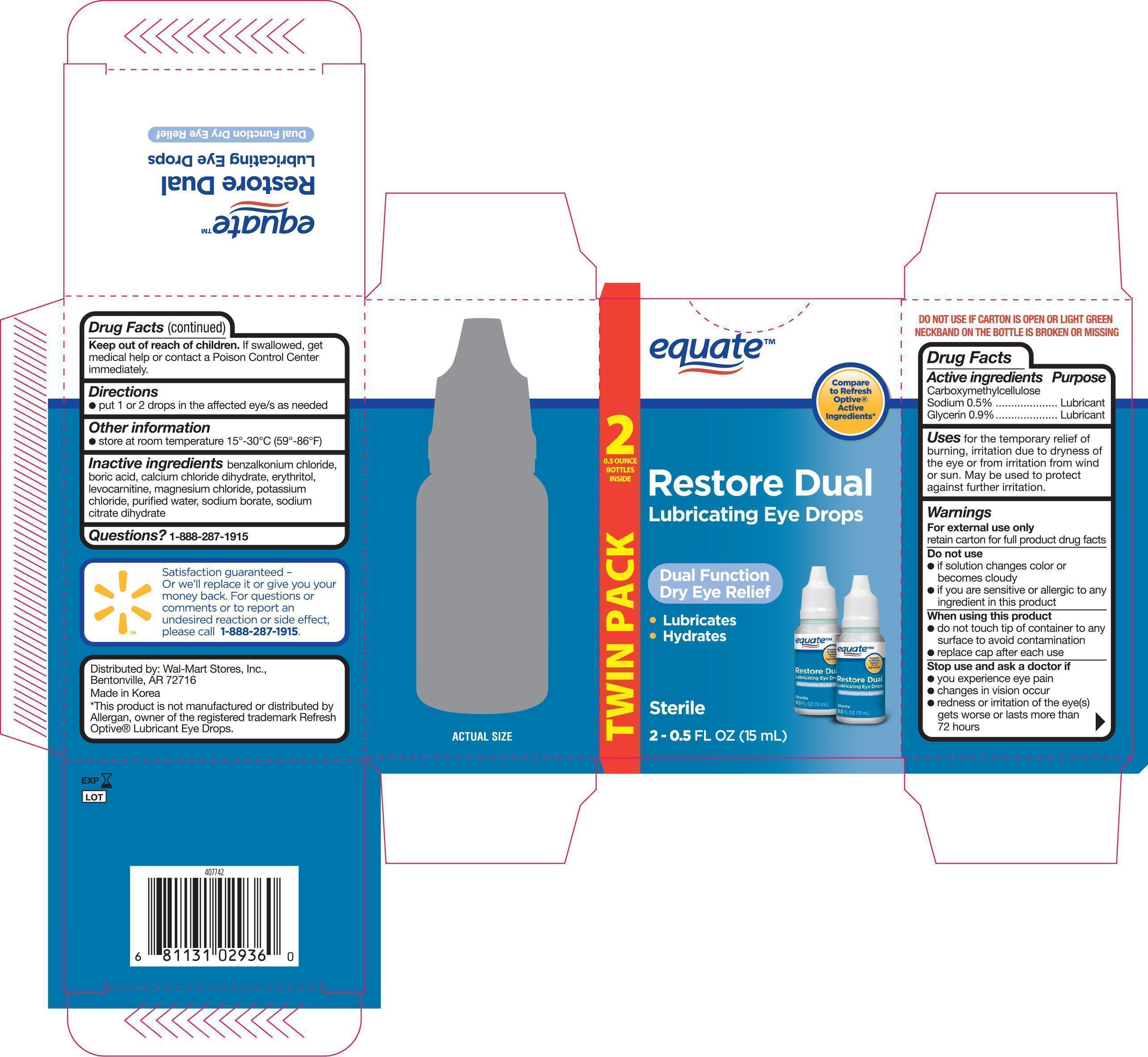 DRUG LABEL: EQUATE LUBRICATING EYE
NDC: 49035-936 | Form: SOLUTION/ DROPS
Manufacturer: WAL-MART STORES INC.
Category: otc | Type: HUMAN OTC DRUG LABEL
Date: 20150121

ACTIVE INGREDIENTS: CARBOXYMETHYLCELLULOSE SODIUM 5 mg/1 mL; GLYCERIN 9 mg/1 mL
INACTIVE INGREDIENTS: BENZALKONIUM CHLORIDE; BORIC ACID; CALCIUM CHLORATE DIHYDRATE; ERYTHRITOL; LEVOCARNITINE; MAGNESIUM CHLORIDE; POTASSIUM CHLORIDE; WATER; SODIUM BORATE

Active ingredients Purpose

Carboxymethylcellulose Sodium 0.5%------------------------- Lubricant

Glycerin 0.9%--------------------------------------------------- Lubricant

Uses

- For the temporary relief of burning, irritation due to dryness of the eye or from irritation from wind or sun
- May be used to protect against further irritation

Warnings

- For external use only

retain carton for full product drug facts

Do not use

- if solution changes color or becomes cloudy
- if you are sensitive or allergic to any ingredient in this product

When using this product

- do not touch tip of container to any surface to avoid contamination
- replace cap after each use

Stop use and ask a doctor if

- you experience eye pain
- changes in vision occur
- redness or irritation of the eye(s) gets worse or lasts more than 72 hours

Keep out of reach of children. If swallowed, get medical help or contact a Poison Control Center immediately.

Directions

- put 1 or 2 drops in the affected eye/s as needed.

Other information

- store at room temperature 15o-30oC (59o-86oF)

Inactive ingredients

benzalkonium chloride, boric acid, calcium chloride dihydrate, erythritol, levocarnitine, magnesium chloride, potassium chloride, purified water, sodium borate, sodium citrate dihydrate

DOSAGE AND ADMINISTRATION

Distributed by:

Wal-Mart Stores, Inc.,

Bentonville, AR 72716

Made in Korea